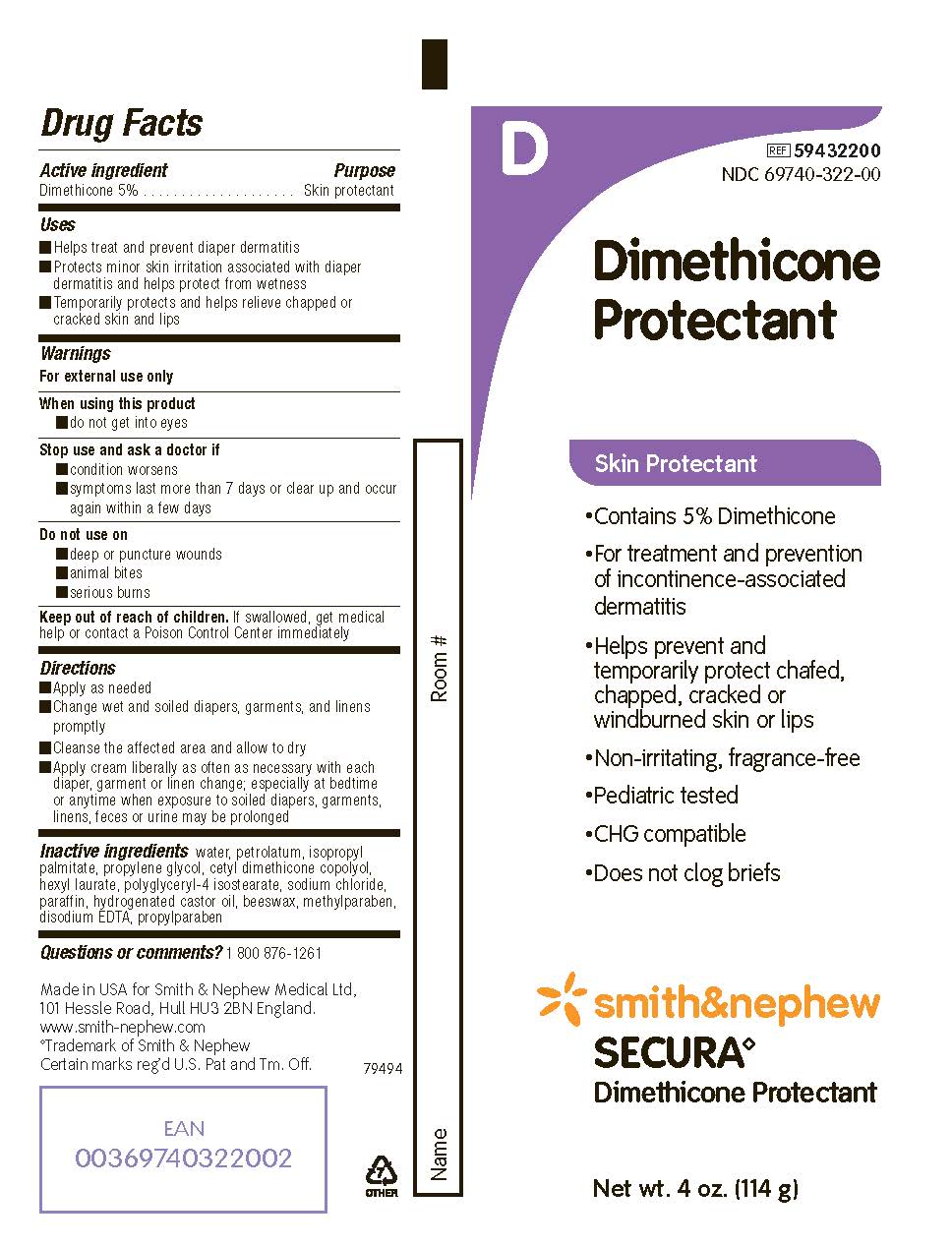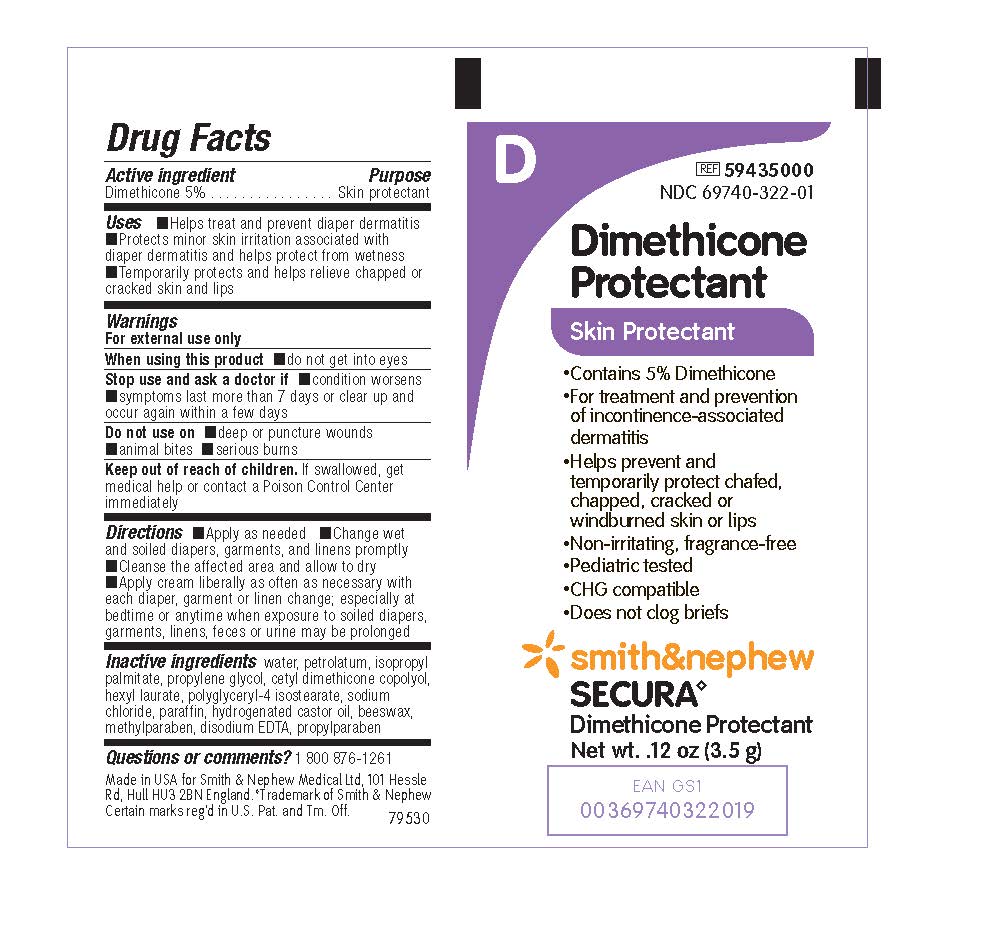 DRUG LABEL: Secura Dimethicone Protectant
NDC: 69740-322 | Form: CREAM
Manufacturer: Smith & Nephew Medical Ltd
Category: otc | Type: HUMAN OTC DRUG LABEL
Date: 20241216

ACTIVE INGREDIENTS: DIMETHICONE 50 mg/1 g
INACTIVE INGREDIENTS: HEXYL LAURATE; ISOPROPYL PALMITATE; METHYLPARABEN; EDETATE DISODIUM; PARAFFIN; PETROLATUM; PROPYLENE GLYCOL; PROPYLPARABEN; SODIUM CHLORIDE; WATER; YELLOW WAX; POLYGLYCERYL-4 ISOSTEARATE; HYDROGENATED CASTOR OIL; CETYL PEG/PPG-10/1 DIMETHICONE (HLB 5)

Secura Dimethicone Protectant

ACTIVE INGREDIENTS

Dimethicone 5%

PURPOSE

Skin protectant

USES

- Helps treat and prevent diaper dermatitis
- Protects minor skin irritation associated with diaper dermatitis and helps protect from wetness
- Temporarily protects and helps relieve chapped or cracked skin and lips

WARNINGS

For external use only

When using this product

- do not get into eyes

Stop use and ask a doctor if

- condition worsens
- symptoms last more than 7 days or clear up and occur again within a few days

Do not use on

- deep or puncture wounds
- animal bites
- serious burns

Keep out of reach of children

- If swallowed, get medical help or contact a Poison Control Center immediately

DIRECTIONS

- Apply as needed
- Change wet and soiled diapers, garments, and linens promptly
- Cleanse the affected area and allow to dry
- Apply cream liberally as often as necessary with each diaper, garment or linen change; especially at bedtime or anytime when exposure to soiled diapers, garments, linens, feces, or urine may be prolonged

INACTIVE INGREDIENTS

water, petrolatum, isopropyl palmitate, propylene glycol, cetyl dimethicone copolyol, hexyl laurate, polyglycerol-4 isostearate, sodium chloride, paraffin, hydrogenated castor oil, beeswax, methylparaben, disodium EDTA, propylparaben

QUESTION OR COMMENTS?

1 800 876-1261

PACKAGE LABEL

PACKAGE LABEL - PRINCIPAL DISPLAY PANEL- TUBE (3.5 g)

Item #59435000

NDC 69740-322-01

Dimethicone Protectant

Skin Protectant

- Contains 5% Dimethicone
- For treatment and prevention of incontinence-associated dermatitis
- Helps prevent and temporarily protect, chafed, chapped, cracked or windburned skin or lips
- Non-irritating, fragrance-free
- Pediatric tested
- CHG Compatible
- Does not clog briefs

Smith & Nephew

Secura◊

Dimethicone Protectant

Made in the USA for Smith & Nephew Medical Ltd, 101 Hessle Road, Hull, HU3 2BN, England

Certain marks reg'd in U.S. Pat and Tm Off.

PACKAGE LABEL - PRINCIPAL DISPLAY PANEL- TUBE (114 g)

Item #59432200

NDC 69740-322-00

Dimethicone Protectant

Skin Protectant

- Contains 5% Dimethicone
- For treatment and prevention of incontinence-associated dermatitis
- Helps prevent and temporarily protect chafed, chapped, cracked, or windburned skin or lips
- Non-irritating, fragrance-free
- Pediatric tested
- CHG Compatible
- Does not clog briefs

Smith & Nephew

Secura◊

Dimethicone Protectant

Made in the USA for Smith & Nephew Medical Ltd, 101 Hessle Road, Hull, HU3 2BN, England.

www.smith-nephew.com

Trademark of Smith & Nephew.

Certain marks reg'd U.S. Pat and Tm. Off.